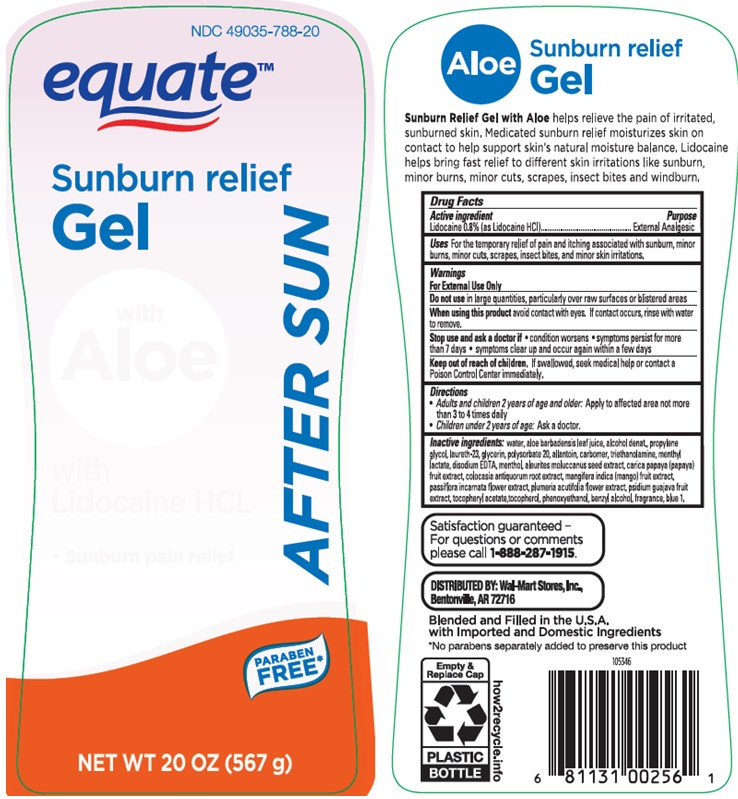 DRUG LABEL: EQUATE Sunburn relief with Aloe After Sun
NDC: 49035-788 | Form: GEL
Manufacturer: Wal-Mart Stores Inc
Category: otc | Type: HUMAN OTC DRUG LABEL
Date: 20241016

ACTIVE INGREDIENTS: LIDOCAINE 8 mg/1 g
INACTIVE INGREDIENTS: MANGO; ALCOHOL; PROPYLENE GLYCOL; LAURETH-23; GLYCERIN; POLYSORBATE 20; ALLANTOIN; CARBOMER INTERPOLYMER TYPE A (ALLYL SUCROSE CROSSLINKED); TROLAMINE; MENTHYL LACTATE, (-)-; EDETATE DISODIUM; LEVOMENTHOL; KUKUI NUT OIL; PAPAYA; COLOCASIA ESCULENTA ROOT; PASSIFLORA INCARNATA FLOWER; GUAVA; .ALPHA.-TOCOPHEROL ACETATE; .ALPHA.-TOCOPHEROL, DL-; PHENOXYETHANOL; BENZYL ALCOHOL; FD&C BLUE NO. 1; ALOE VERA LEAF; WATER; PLUMERIA ALBA FLOWER OIL

Equate Sunburn Relief with Aloe After Sun Gel

Active ingredient

Lidocaine 0.8% (as Lidocaine HCI)

Purpose

External Analgesic

Uses

For the temporary relief of pain and itching associated with sunburn, minor burns, minor cuts, scrapes, insect bites, and minor skin irritations

Warnings

For External Use Only

Do not use

in large quantities, particularly over raw surfaces or blistered areas

When using this product

avoid contact with eyes. If contact occurs, rinse with water to remove.

Stop use and ask a doctor if

• condition worsens • symptoms persist for more than 7 days • symptoms clear up and occur again within a few days

Keep out of reach of children

If swallowed, seek medical help or contact a Poison Control Center immediately.

Directions

• Adults and children 2 years of age and older: Apply to affected area not more than 3 to 4 times daily

• Children under 2 years of age: Ask a doctor.

Inactive ingredients

water, aloe barbadensis leaf juice, alcohol denat., propylene glycol, laureth-23, glycerin, polysorbate 20, allantoin, carbomer, triethanolamine, menthyl lactate, disodium EDTA, menthol, aleurites moluccanus seed extract, carica papaya (papaya) fruit extract, colocasia antiquorum root extract, mangifera indica (mango) fruit extract, passiflora incarnata flower extract, plumeria acutifolia flower extract, psidium guajava fruit extract, tocopheryl acetate, tocopherol, phenoxyethanol, benzyl alcohol, fragrance, blue 1.